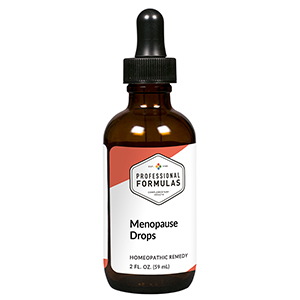 DRUG LABEL: Menopause Drops
NDC: 63083-2044 | Form: LIQUID
Manufacturer: Professional Complementary Health Formulas
Category: homeopathic | Type: HUMAN OTC DRUG LABEL
Date: 20190815

ACTIVE INGREDIENTS: ARTEMISIA ANNUA FLOWERING TOP 3 [hp_X]/59 mL; DIOSCOREA VILLOSA TUBER 3 [hp_X]/59 mL; CHASTE TREE FRUIT 3 [hp_X]/59 mL; BOS TAURUS OVARY 6 [hp_X]/59 mL; BLACK COHOSH 12 [hp_X]/59 mL; ESTROGENS, CONJUGATED 12 [hp_X]/59 mL; SANGUINARIA CANADENSIS ROOT 12 [hp_X]/59 mL; LACHESIS MUTA VENOM 16 [hp_X]/59 mL
INACTIVE INGREDIENTS: ALCOHOL; WATER

C44

ACTIVE INGREDIENTS

Chamomilla 3X
Dioscorea villosa 3X
Agnus castus 3X, 6X
Ovary 6X
Cimicifuga racemosa 12X
Estrogen 12X
Sanguinaria canadensis 12X
Lachesis mutus 16X

QUESTIONS

Professional Formulas

PO Box 2034 Lake Oswego, OR 97035

INDICATIONS

For the temporary relief of hot flashes, sweating, irritability, difficulty sleeping, or fatigue.*

PURPOSE

*Claims based on traditional homeopathic practice, not accepted medical evidence. Not FDA evaluated.

WARNINGS

In case of overdose, get medical help or contact a poison control center right away.

Keep out of the reach of children.

PREGNANCY OR BREAST FEEDING

If pregnant or breastfeeding, ask a healthcare professional before use.

DIRECTIONS

Place drops under tongue 30 minutes before/after meals. Adults and children 12 years and over: Take 10 drops up to 3 times per day. Consult a physician for use in children under 12 years of age. Not intended for use in infants.

OTHER INFORMATION

Tamper resistant. If seal is broken, do not use. After opening, close container tightly and store at room temperature away from heat.

INACTIVE INGREDIENTS

20% ethanol, purified water.

LABEL

Est 1985

Professional Formulas

Complementary Health

Menopause Drops

Homeopathic Remedy

2 FL. OZ. (59 mL)